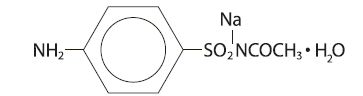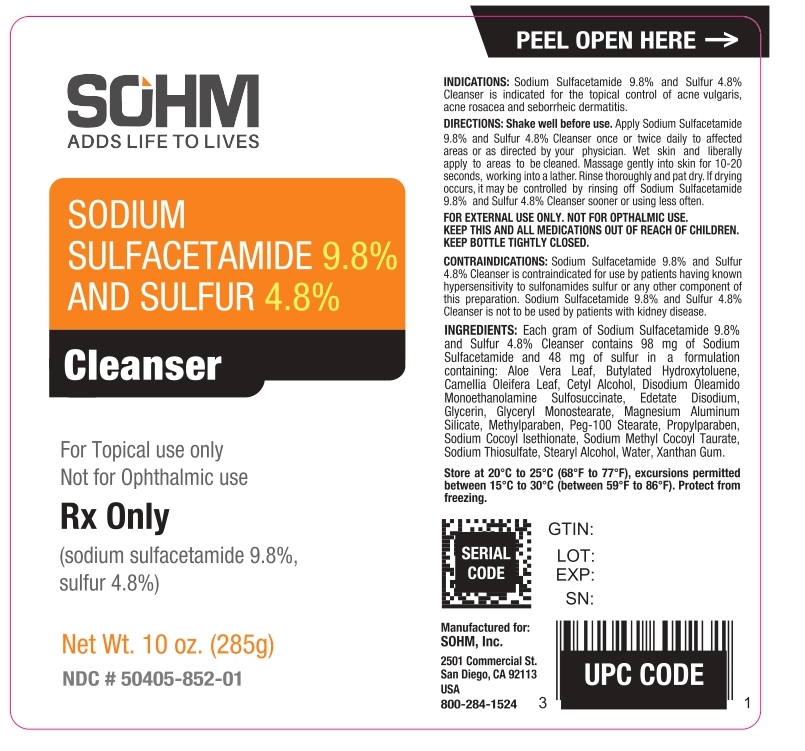 DRUG LABEL: Sodium Sulfacetamide 9.8 % and Sulfur 4.8 % Cleanser
NDC: 50405-852 | Form: LOTION
Manufacturer: SOHM, Inc
Category: prescription | Type: HUMAN PRESCRIPTION DRUG LABEL
Date: 20230503

ACTIVE INGREDIENTS: SULFACETAMIDE SODIUM 98 mg/1 g; SULFUR 48 mg/1 g
INACTIVE INGREDIENTS: ALOE VERA LEAF; BUTYLATED HYDROXYTOLUENE; CAMELLIA OLEIFERA LEAF; CETYL ALCOHOL; DISODIUM OLEAMIDO MEA-SULFOSUCCINATE; EDETATE DISODIUM; GLYCERIN; GLYCERYL MONOSTEARATE; MAGNESIUM ALUMINUM SILICATE; METHYLPARABEN; PEG-100 STEARATE; PROPYLPARABEN; SODIUM COCOYL ISETHIONATE; SODIUM METHYL COCOYL TAURATE; SODIUM THIOSULFATE; STEARYL ALCOHOL; WATER; XANTHAN GUM

Sodium Sulfacetamide 9.8% - Sulfur 4.8% Cleanser

For Topical use only

Not for Ophthalmic use

Rx Only

DESCRIPTION:

Sulfacetamide Sodium is a sulfonamide with antibacterial activity while Sulfur acts as a keratolytic agent. Chemically Sulfacetamide Sodium is N-[(4-aminophenyl) sulfonyl]-acetamide, monosodium salt, monohydrate. The structural formula is:

Each gram of Sodium Sulfacetamide 9.8% and Sulfur 4.8% Cleanser contains 98 mg of Sodium Sulfacetamide and 48 mg of sulfur in a formulation containing: Aloe Vera Leaf, Butylated Hydroxytoluene, Camellia Oleifera Leaf, Cetyl Alcohol, Disodium Oleamido Monoethanolamine Sulfosuccinate, Edetate Disodium, Glycerin, Glyceryl Monostearate, Magnesium Aluminum Silicate, Methylparaben, Peg-100 Stearate, Propylparaben, Sodium Cocoyl lsethionate, Sodium Methyl Cocoyl Taurate, Sodium Thiosulfate, Stearyl Alcohol, Water, Xanthan Gum.

CLINICAL PHARMACOLOGY:

The most widely accepted mechanism of action of sulfonamides is the Woods-Fildes theory, which is based on the fact that sulfonamides act as competitive antagonists to para-aminobenzoic acid (PABA), an essential component for bacterial growth. While absorption through intact skin has not been determined, sulfacetamide sodium is readily absorbed from the gastrointestinal tract when taken orally and excreted in the urine, largely unchanged. The biological half-life has variously been reported as 7 to 12.8 hours. The exact mode of action of sulfur in the treatment of acne is not known, but it has been reported that it inhibits the growth of Propionibacterium acnes and the formation of free fatty acids.

INDICATIONS AND USAGE

INDICATIONS: Sulfacetamide Sodium and Sulfur Cleanser is indicated in the topical control of acne vulgaris, acne rosacea and seborrheic dermatitis.

CONTRAINDICATIONS

CONTRAINDICATIONS: Sulfacetamide Sodium and Sulfur Cleanser is contraindicated for use by patients having known hypersensitivity to sulfonamides, sulfur or any other component of this preparation. Sulfacetamide Sodium and Sulfur Cleanser is not to be used by patients with kidney disease.

WARNINGS:

Although rare, sensitivity to Sulfacetaminde Sodium may occur. Therefore, caution and careful supervision should be observed when prescribing this drug for patients who may be prone to hypersensitivity to topical sulfonamides. Systemic toxic reactions such as agranulocytosis, acute hemolytic anemia, purpura hemorrhagica, drug fever, jaundice and contact dermatitis indicate hypersensitivity to sulfonamides. Particular caution should be employed if areas of denuded or abraded skin are involved.

FOR EXTERNAL USE ONLY. Keep away from eyes. Keep out of reach of children. Keep container tightly closed.

PRECAUTIONS:

GENERAL PRECAUTIONS

General -If irritation develops, use of the product should be discontinued and appropriate therapy instituted. Patients should be carefully observed for possible local irritation or sensitization during long-term therapy. The object of this therapy is to achieve desquamation without irritation, but Sulfacetamide Sodium and Sulfur can cause reddening and scaling of the epidermis. These side effects are not unusual in the treatment of acne vulgaris, but patients should be cautioned about the possibility.

PATIENT COUNSELING INFORMATION

Information for patients - Avoid contact with eyes, eyelids, lips and mucous membranes. If accidental contact occurs, rinse with water. If excessive irritation develops, discontinue use and consult your physician.

CARCINOGENESIS AND MUTAGENESIS AND IMPAIRMENT OF FERTILITY

Carcinogenesis, Mutagenesis and Impairment of Fertility - Long-term studies in animals have not been performed to evaluate carcinogenic potential.

PREGNANCY

Pregnancy: Category C - Animal reproduction studies have not been conducted with Sulfacetamide Sodium and Sulfur lotion. It is also not known whether Sulfacetamide Sodium and Sulfur cleanser can cause fetal harm when administered to a pregnant woman or can affect reproduction capacity. Sulfacetamide Sodium and Sulfur cleanser should be given to a pregnant woman only if clearly needed.

NURSING MOTHERS

Nursing Mothers - It is not known whether sulfacetamide sodium is excreted in the human milk following topical use of Sulfacetamide Sodium and Sulfur lotion. However, small amounts of orally administered sulfonamides have been reported to be eliminated in human milk. In view of this and because many drugs are excreted in human milk, caution should be exercised when Sulfacetamide Sodium and Sulfur cleanser is administered to a nursing woman.

PEDIATRIC USE

Pediatric Use - Safety and effectiveness in children under the age of 12 have not been established.

ADVERSE REACTIONS

ADVERSE REACTIONS: Although rare, Sulfacetamide Sodium may cause local irritation.

DOSAGE AND ADMINISTRATION: Use once daily or as directed by your physician. Wet skin. Apply in a film to entire face, avoiding contact with eyes or mucous membranes. Wait 10 minutes or until dry. Rinse thoroughly with water and pat dry.

HOW SUPPLIED:

Sulfacetamide Sodium 9.8% and Sulfur 4.8% cleanser is supplied in
10 oz (285 g) bottle NDC #50405-852-01

STORAGE AND HANDLING

Store at 20°-25°C (68°-77°F), excursions permitted between 15°-30°C (59°-86°F). Brief exposure to temperatures up to 40° (104°F) may be tolerated provided the mean kinetic temperature does not exceed 25°C(77°F); however such exposure should be minimized. Protect from freezing.

Call your doctor about side effects. You may report side effects to FDA at 1-800-FDA-1088.
KEEP THIS AND ALL MEDICATIONS OUT OF THE REACH OF CHILDREN

Rx Only

Manufactured for: SOHM, Inc. 2501 Commercial St., San Diego, CA 92113 USA

For any product questions or concerns please call: 800-284-1524
Rev. 04-2023

PRINCIPAL DISPLAY PANEL - 285 g Bottle Label

NDC 50405-852-01

Sodium Sulfacetamide 9.8% and Sulfur 4.8% Cleanser

Rx Only

10 oz (285 g)